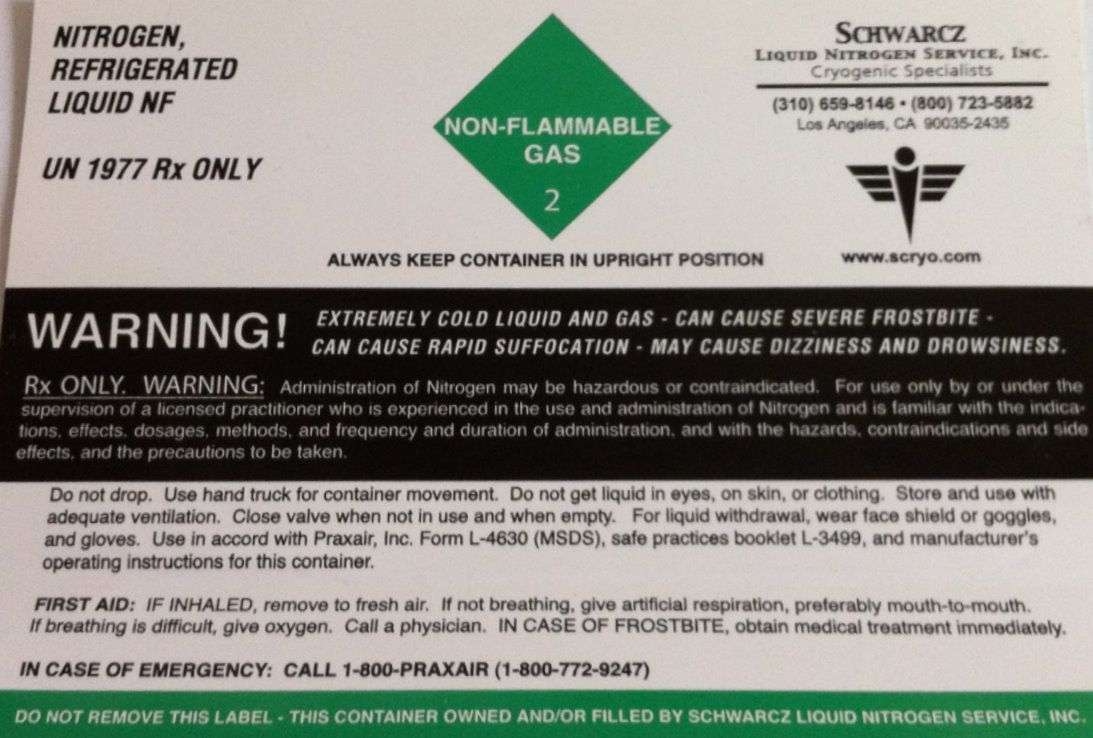 DRUG LABEL: Nitrogen, Refrigerated
NDC: 42392-001 | Form: LIQUID
Manufacturer: Schwarcz Liquid Nitrogen Service, Inc.
Category: prescription | Type: HUMAN PRESCRIPTION DRUG LABEL
Date: 20120201

ACTIVE INGREDIENTS: NITROGEN 1 L/1 L

Nitrogen, Refrigerated Liquid

PACKAGE LABEL

NITROGEN,

REFRIGERATED

LIQUID NF

UN 1977 Rx ONLY

NON-FLAMMABLE
GAS
2
SCHWARCZ
LIQUID NITROGEN SERVICE, INC.
CRYOGENIC SPECIALISTS
(310) 659-8146
(800) 723-5882
LOS ANGELES, CA 90035-2435
ALWAYS KEEP CONTAINER IN UPRIGHT POSITION
WWW.SCRYO.COM
WARNING! EXTREMELY COLD LIQUID GAS
CAN CAUSE SEVERE FROSTBITE
CAN CAUSE RAPID SUFFOCATION
MAY CAUSE DIZZINESS AND DROWSINESS
Rx ONLY
WARNING: Administration of Nitrogen may be hazardous or contraindicated. For use only by or under the supervision of a licensed practitioner who is experienced in the use and administration of Nitrogen and is familiar with the indications, effects, dosages, methods, and frequency and duration of administration, and with the hazards, contraindications and side effects, and the precautions to be taken.
Do not drop. Use hand truck for container movement. Do not get liquid in eyes, on skin, or clothing. Store and use with adequate ventilation. Close valve when not in use and when empty. For liquid withdrawal, wear face shield or goggles, and gloves. Use in accord with Praxair, Inc. Form L-4630 (MSDS), safe practices booklet l-3499, and manufacturer's operating instructions for this container.
FIRST AID: IF INHALED, remove to fresh air. If not breathing, give artificial respiration, preferably mouth-to-mouth. If breathing is difficult, give oxygen.